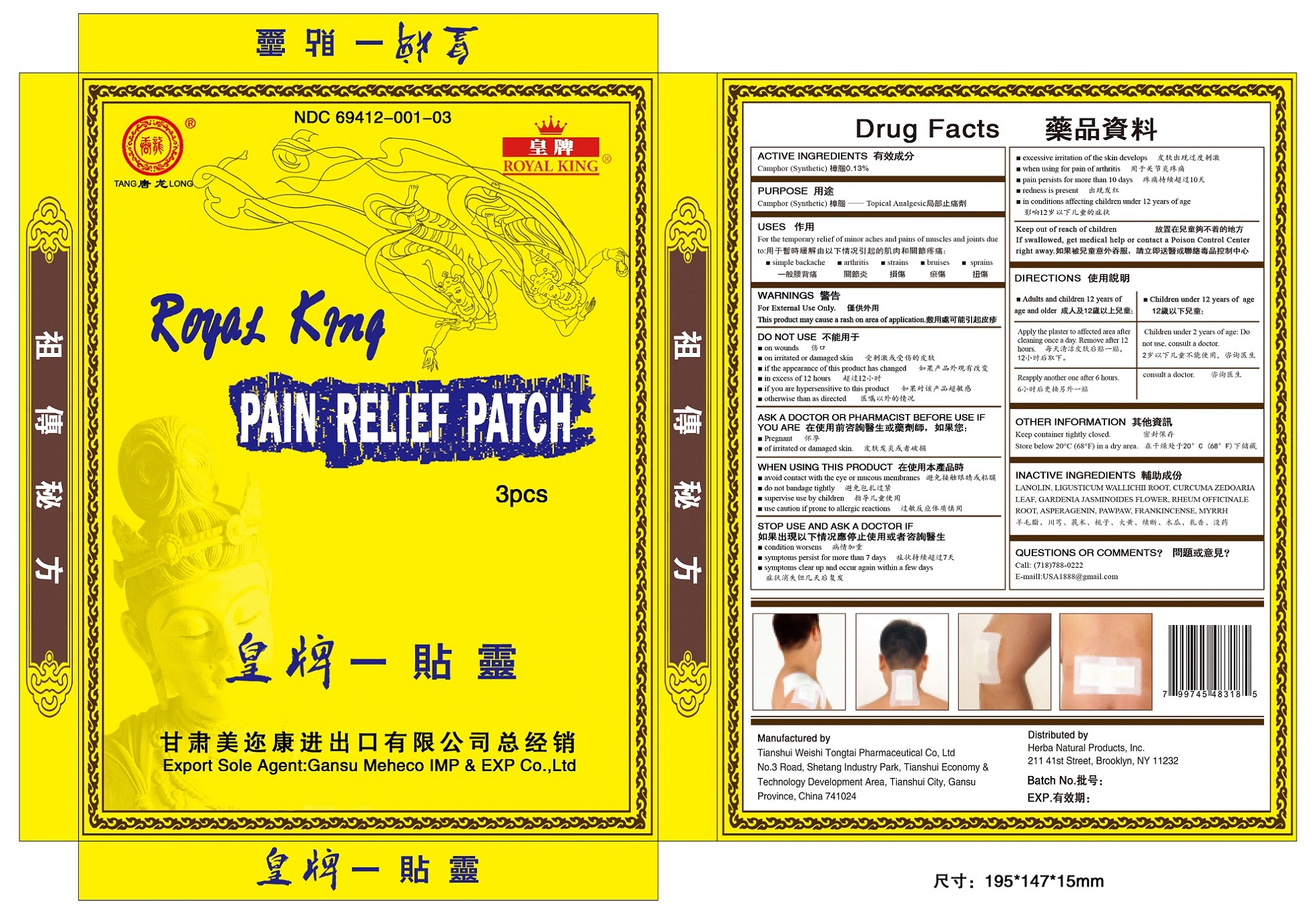 DRUG LABEL: Royal King Pain Relief Patch
NDC: 69412-001 | Form: PATCH
Manufacturer: Tianshui Weishi Tongtai Pharmaceutical Co Ltd
Category: otc | Type: HUMAN OTC DRUG LABEL
Date: 20211129

ACTIVE INGREDIENTS: CAMPHOR (SYNTHETIC) 0.13 g/100 g
INACTIVE INGREDIENTS: LANOLIN; LIGUSTICUM WALLICHII ROOT; CURCUMA ZEDOARIA LEAF; GARDENIA JASMINOIDES FLOWER; RHEUM OFFICINALE ROOT; ASPERAGENIN; PAWPAW; FRANKINCENSE; MYRRH

Tianshui Weishi Tongtai Pharmaceutical Co Ltd

ACTIVE INGREDIENTS

Camphor (Synthetic) 0.13%

PURPOSE

Camphor (Synthetic) Topical Analgesic

USES

For the temporary relief of minor aches and pains of muscles and joints due to:

simple backache

arthritis

strains

bruises

sprains

WARNINGS

For External Use only.

This product may cause a rash on area of application.

DO NOT USE

on wounds

on irritated or damaged skin

if the appearance of this product has changed

in excess of 12 hours

if you are hypersensitive to this product

otherwise than as directed

ASK A DOCTOR OR PHARMACIST BEFORE USE IF YOU ARE

pregnant

of irritated or damaged skin.

WHEN USING THIS PRODUCT

avoid contact with the eye or mucous membranes

do not bandage tightly

supervise use by children

use caution if prone to allergic reactions

STOP USE AND ASK A DOCTOR IF

condition worsens

symptoms persist for more than 7 days

symptoms clear up and occur again within a few days

excessive irritation of the skin develops

when using for pain of arthritis

pain persists for more than 10 days

redness is present

in conditions affecting children under 12 years of age

KEEP OUT OF REACH OF CHILDREN

If swallowed, get medical help or contact a Poison Control Center right away.

DIRECTIONS

Adults and children 12 years of age and older: Apply the plaster to affected area after cleaning once a day. Remove after 12 hours.
Reapply another one after 6 hours. Children under 12 years of age, consult a doctor. Children under 2 years of age: Do not use, consult a doctor.

OTHER INFORMATION

Keep container tightly closed.

Store below 20°C (68°F) in a dry area.

INACTIVE INGREDIENTS

LANOLIN, LIGUSTICUM WALLICHII ROOT, CURCUMA ZEDOARIA LEAF, GARDENIA JASMINOIDES FLOWER, RHEUM OFFICINALE ROOT, ASPERAGENIN, PAWPAW, FRANKINCENSE, MYRRH

QUESTIONS OR COMMENTS

Manufactured by Tianshui Weishi Tongtai Pharmaceutical Co, Ltd

No.3 Road, Shetang Industry Park, Tianshui Economy & Technology Development Area, Tianshui City, Gansu Province, China 741024

Distributed by Herba Natural Products, Inc.

211 41st Street, Brooklyn, NY 11232

Phone: (718)788-0222